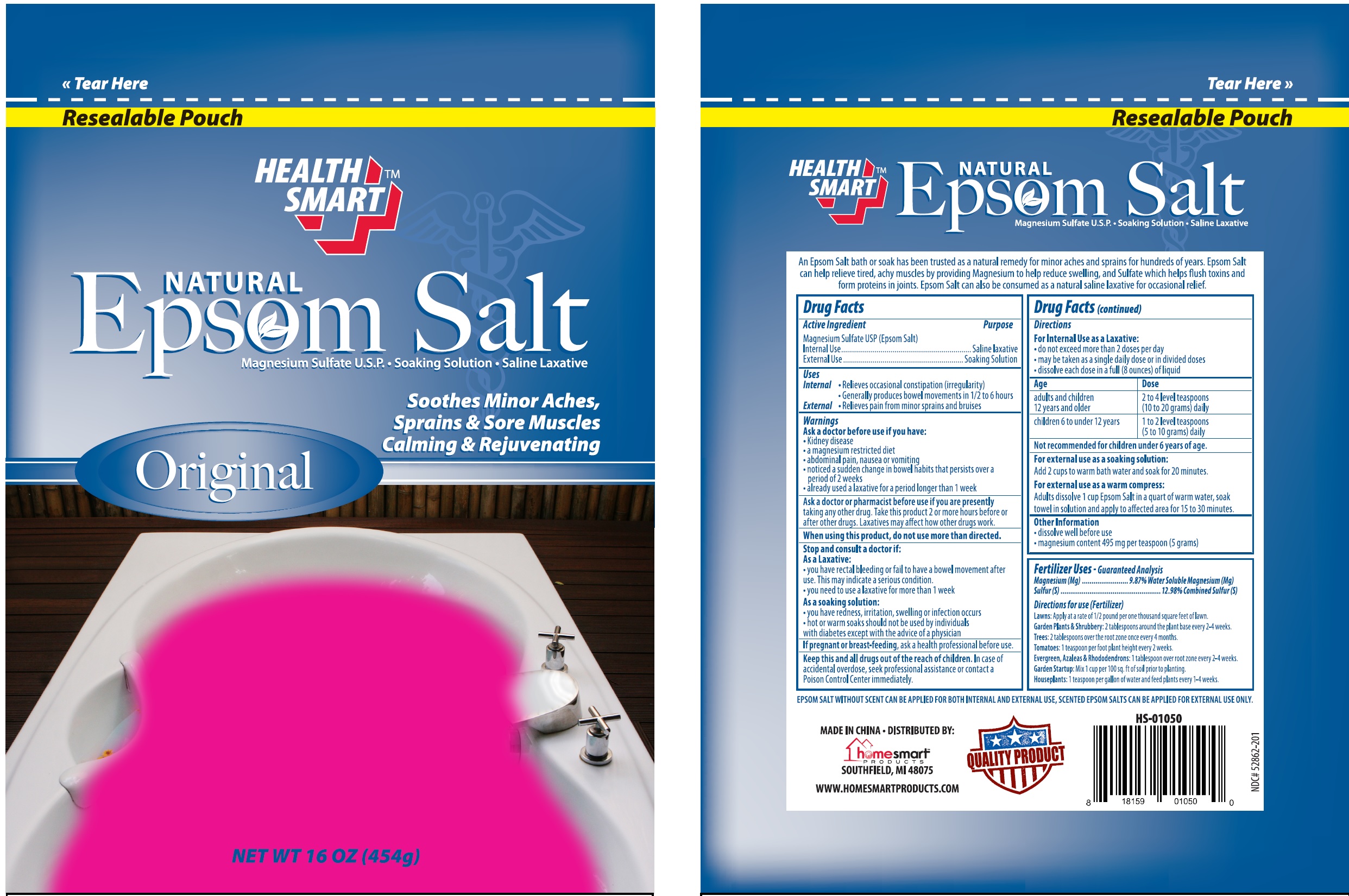 DRUG LABEL: Health Smart Natural Epsom Salt
NDC: 52862-201 | Form: GRANULE, FOR SOLUTION
Manufacturer: International Wholesale, Inc.
Category: otc | Type: HUMAN OTC DRUG LABEL
Date: 20130715

ACTIVE INGREDIENTS: MAGNESIUM SULFATE 1 g/1 g

Drug Facts

Active Ingredient

Magnesium Sulfate USP (Epsom Salt)

Purpose

Internal Use.......... Saline Laxative

External Use..........Soaking Solution

Uses

Internal

- Relieves occasional constipation (irregularity)
- Generally produces bowel movements in 1/2 to 6 hours

External

- Relieves pain from major sprains and bruises

Warnings

Ask a doctor before use if you have:

- Kidney disease
- a magnesium restricted diet
- abdominal pain, nausea or vomiting
- noticed a sudden change in bowel habbits that persists over a period of 2 weeks
- already used a laxative for a period longer than 1 week

Ask a doctor or pharmacist before use if you are presently taking any other drug. Take this product 2 or more hours before or after other drugs. Laxatives may affect how other drugs work.

Stop and consult a doctor if:

As Laxative:

- you have rectal bleeding or fail to have a bowel movement after use. This may indicate a serious condition
- you need to use a laxative for more than 1 week

As soaking solution:

- you have redness, irritation, swelling or infection occurs
- hot or warm soaks should not be used by individuals with diabeties except with the advice of a physician

PREGNANCY OR BREAST FEEDING

If pregnant or breast-feeding, ask a health profesional before use.

KEEP OUT OF REACH OF CHILDREN

Keep this and all drugs out of the reach of children. In the case of an accidental overdose, seek professional assistance or contact a Poison Control Center immedietly.

Directions

for Internal Use as a Laxative:

- do not exceed more than 2 doses per day
- may be taken as a single daily dose or in divided doses
- dissolve each dose in a full (8 ounces) of liquid

Age | Dose
adults and children 12 years and older | 2 to 4 level teaspoons (10 to 20 grams) daily
children 6 to under 12 years | 1 to 2 level teaspoons (5 to 10 grams) daily

Not recomended for children under 6 years of age

DOSAGE AND ADMINISTRATION

For external use as a soaking solution:

Add two cups to warm bath water and soak for 20 minutes.

For external use as a compress:

Adults dissolve 1 cup Epsom Salt in a quart of warm water, soak towel in solution and apply to affected area for 15 to 30 minutes.

Other Information

- dissolve well before use
- magnesium content 495 mg per teaspoon (5 grams)

Fertilizer Uses - Guaranteed Analysis

Magnesium (Mg)..................9.87% Water Soluble Magnesium (Mg)

Sulfer(S).................................................12.98%Combined Sulfer(S)

Directions for use (Fertilizer)

Lawns: Apply at a rate of 1/2 pound per one thousand square feet of lawn.

Garden Plants & Shrubbery: 2 tablespoons around the plant base every 2-4 weeks.

Trees: 2 tablespoons over the root zone every 4 months.

Tomatoes: 1 teaspoon per foot plant height every 2 weeks.

Evergreen, Azaleas & Rhododendrons: 1 tablespoon over root zone every 2-4 weeks.

Garden Startup: Mix 1 cup per 100 sq. ft of soil prior to planting.

Houseplants: 1 teaspoon per gallon of water and feed plants every 1-4 weeks.

An Epsom Salt bath or soak has been trusted as a natural remedy for minor aches and sprains for hundreds of years. Epsom Salt can help relieve tired, achy muscles by providing Magnesium to help reduce swelling, and Sulfate which helps flush toxins from proteins in joints. Epsom Salt can also be consumed as a natural saline laxative for occassional relief.

EPSOM SALT WITHOUT SCENT CAN BE APPLIED FOR BOTH INTERNAL AND EXTERNAL USE, SCENTED EPSOM SALTS CAN BE APPLIED FOR EXTERNAL USE ONLY.

MADE IN CHINA . DISTRIBUTED BY:
homesmartTM
PRODUCTS
SOUTHFIELD, MI 48075
WWW.HOMESMARTPRODUCTS.COM
NDC#52862-201

Package Label

HEALTH
SMARTTM

NATURAL
Epson Salt

Magnesium Sulfate U.S.P • Soaking Solution • Saline Laxative

Soothes Minor Aches,
Sprains & Sore Muscles
Calming & Rejuvenating

Original

NET WT 16 OZ (454g)